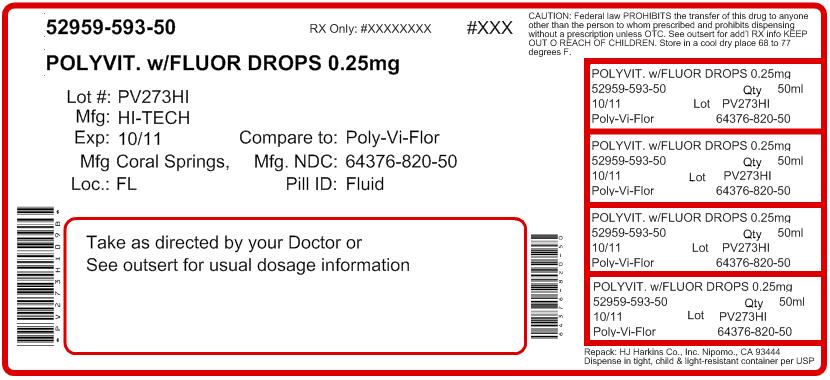 DRUG LABEL: Multi-Vitamin Fluoride Drops
                        
NDC: 52959-593 | Form: SOLUTION
Manufacturer: H.J. Harkins Company, Inc.
Category: prescription | Type: HUMAN PRESCRIPTION DRUG LABEL
Date: 20111025

ACTIVE INGREDIENTS: VITAMIN A 1500 [iU]/1 mL; THIAMINE 0.5 mg/1 mL; RIBOFLAVIN 0.6 mg/1 mL; ASCORBIC ACID 35 mg/1 mL; CHOLECALCIFEROL 400 [iU]/1 mL; NIACIN 8 mg/1 mL; PYRIDOXINE 0.4 mg/1 mL; CYANOCOBALAMIN 2 ug/1 mL; FLUORIDE ION 0.25 mg/1 mL; .ALPHA.-TOCOPHEROL SUCCINATE, D- 5 [iU]/1 mL
INACTIVE INGREDIENTS: SODIUM HYDROXIDE; SODIUM BENZOATE; WATER; POLYSORBATE 80; METHYLPARABEN; GLYCERIN; ORANGE OIL; FERROUS SULFATE; CHERRY; CARAMEL

Unknown Title

MULTI-VITAMIN FLUORIDE DROPS
0.25 mg per mL
Rx Only

DESCRIPTION

Each 1.0 mL supplies: |  | Percentage of U.S. Recommended Daily Allowance Children 6 mos to 4 years old
Vitamin A (as Vitamin A palmitate) | 1500 IU | 60%
Vitamin C (as Ascorbic Acid) | 35 mg | 88%
Vitamin D (as Cholecalciferol) | 400 IU | 100%
Vitamin E (as D-Alpha-Tocopheryl Acid Succinate) | 5 IU | 50%
Vitamin B1 (as Thiamine HCl) | 0.5 mg | 71%
Vitamin B2 (as Riboflavin Phosphate Sodium) | 0.6 mg | 75%
Vitamin B12 (as Cyanocobalamine) | 2 mcg | 67%
Niacin (as Niacinamide) | 8 mg | 89%
Vitamin B6 (as Pyridoxine HCl) | 0.4 mg | 57%
Fluoride (as Sodium Fluoride) | 0.25 mg | *
* Daily Value not established
See INDICATIONS AND USAGE section for use by children 6 months to 6 years of age.
This product does not contain the essential vitamin folic acid.

Active ingredient for caries prophylaxis: Fluoride as sodium fluoride. Does not contain folic acid.

Other ingredients: Caramel color, cherry flavor, ferrous sulfate, oil of orange, glycerin, methylparaben, polysorbate 80, purified water, sodium benzoate and sodium hydroxide.

CLINICAL PHARMACOLOGY

It is well established that fluoridation of water supply (1 ppm fluoride) during the period of tooth development leads to a significant decrease in the incidence of dental caries.

Hydroxyapatite is the principal crystal for all calcified tissue in the human body. The fluoride ion reacts with the hydroxyapatite in the tooth as it is formed to produce the more caries-resistant crystal, fluorapatite.

The reaction may be expressed by the equation:^1

Ca10(PO4)6(OH)2 + 2F- CA10(PO4)6F2 + 2OH-

(Hydroxyapatite) (Fluorapatite)

Three stages of fluoride deposition in tooth enamel can be distinguished:
1. Small amounts (reflecting the low levels of fluoride in tissue fluids) are incorporated into the enamel crystals while they are being formed.

2. After enamel has been laid down, fluoride deposition continues in the surface enamel. Diffusion of fluoride from the surface inward is apparently restricted.

3. After eruption, the surface enamel acquires fluoride from water, food, supplementary fluoride and smaller amounts from saliva.

INDICATIONS AND USAGE

Supplementation of the diet with vitamins A, C and D.
Multi-Vitamin Fluoride Drops 0.25 mg also provide fluoride for caries prophylaxis.

The American Academy of Pediatrics recommends that children up to age 16, in areas where drinking water contains less than optimal levels of fluoride, receive daily fluoride supplementation.

The American Academy of Pediatrics recommend that infants and young children 6 months to 3 years of age, in areas where drinking water contains less than 0.3 ppm of fluoride, and children 3-6 years of age, in areas where the drinking water contains 0.3 through 0.6 ppm of fluoride, receive 0.25 mg of supplemental fluoride daily which is provided in a dose of 1 mL of Multi-Vitamin Fluoride 0.25 mg drops. (see Dosage and Administration).

Multi-Vitamin Fluoride 0.25 mg drops supply significant amounts of vitamins A, C and D to supplement the diet, and to help assure that nutritional deficiencies of these vitamins will not develop. Thus, in a single easy-to-use preparation, children obtain essential vitamins and fluoride.

WARNINGS

As in the case of all medications, keep out of reach of children.

PRECAUTIONS

The suggested dose should not be exceeded since dental fluorosis may result from continued ingestion of large amounts of fluoride.

When prescribing vitamin fluoride products:
1. Determine the fluoride content of the drinking water.

2. Make sure the child is not receiving significant amounts of fluoride from other medications and swallowed toothpaste.

3. Periodically check to make sure that the child does not develop significant dental fluorosis.

Multi-Vitamin and Fluoride Drops 0.25 mg should be dispensed in the original plastic container, since contact with glass leads to instability and precipitation. (The amount of sodium fluoride in the 50 mL size is well below the maximum to be dispensed at one time according to recommendations of the American Dental Association.)

Important Considerations When Using Dosage Schedule:

- If fluoride level is unknown, drinking water should be tested for fluoride content before supplements are prescribed. For testing of fluoride content, contact the local or state health department.
- All sources of fluoride should be evaluated with a thorough fluoride history.
- Patient exposure to multiple water sources can make proper prescribing complex.
- Ingestion of higher than recommended levels of fluoride by children has been associated with an increase in mild dental fluorosis in developing, unerupted teeth.
- Fluoride supplements require long-term compliance on a daily basis.

ADVERSE REACTIONS

Allergic rash and other idiosyncrasies have been rarely reported.

DOSAGE AND ADMINISTRATION

See following chart. May be dropped directly into mouth with dropper; or mixed with cereal, fruit juice or other food.

Fluoride Ion Level in Drinking Water (ppm)*
Age | <0.3 ppm | 0.3-0.6 ppm | >0.6 ppm
Birth - 6 months | None | None | None
6 mos - 3 years | 0.25 mg (1 mL) / day** | None | None
3 - 6 years | 0.50 mg (2 mL) / day | 0.25 mg (1 mL) / day | None
*1.0 ppm = 1 mg/liter
** 2.2 mg sodium fluoride contains 1 mg fluoride ion.

HOW SUPPLIED

Multi-Vitamin and Fluoride 0.25 mg drops is available in 50 mL bottles with accompanying calibrated dropper.

RECOMMENDED STORAGE

Store at controlled room temperature, 15º-25ºC (59º-77ºF). Excursions permitted. After opening, store away from direct light. Close tightly after each use. Occasional deepening of color has no significant effect on vitamin potency.
REFRIGERATION IS NOT REQUIRED.

SHAKE WELL

REFERENCES

1. Brudevoid F, McCann HG: Fluoride and caries control - Mechanism of action, in Nizel AE (ed): The Science of Nutrition and its Application in Clinical Dentistry. Philadelphia, WB Saunders Co, 966, pp 331-347.

2. American Academy of Pediatrics Committee on Nutrition: Fluoride supplementation, Pediatrics 1986;77:758.

3. American Dental Association Council on Dental Therapeutics: Accepted Dental Therapeutics, ed 38, Chicago, 1979, p 321.

4. Hennon DK, Stookey GK, Muhler JC: The clinical anticariogenic effectiveness of supplementary fluoride-vitamin preparations - Results at the end of three years. J Dent Children 1966; 33 January:3-12.

5. Hennon DK, Stookey GK, Muhler JC: The clinical anticariogenic effectiveness of supplementary fluoride-vitamin preparations - Results at the end of four years. J Dent Children 1967; 34\ November;439- 443.

6. Hennon DK, Stookey GK, Muhler JC: The clinical anticariogenic effectiveness of supplementary fluoride-vitamin preparations - Results at the end of five and a half years. Phar and Ther in Dent 1970; 1:1.

7. Hennon DK, Stookey GK, Beiswanger BB: Fluoride-vitamin supplements: Effects on dental caries and fluorosis when used in areas with suboptimum fluoride in the water supply. J Am Dent Assoc 1977; 95-965.

Manufactured for: Boca Pharmacal, Inc. Coral Springs, FL 33065 www.bocapharmacal.com 1-800-354-8460 Rev. 05/11

PACKAGE LABEL.PRINCIPAL DISPLAY PANEL

[Rev 7]